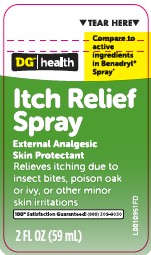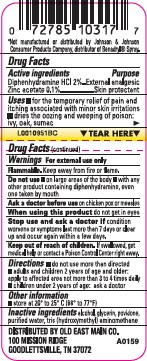 DRUG LABEL: Itch Relief
NDC: 55910-295 | Form: SPRAY
Manufacturer: Old East Main Co.
Category: otc | Type: HUMAN OTC DRUG LABEL
Date: 20260302

ACTIVE INGREDIENTS: DIPHENHYDRAMINE HYDROCHLORIDE 20 mg/1 mL; ZINC ACETATE 1 mg/1 mL
INACTIVE INGREDIENTS: POVIDONE; WATER; TROMETHAMINE; ALCOHOL; GLYCERIN

Dollar General 295.000/295AA-AB
Itch Relief Spray

Active ingredients

Diphenhydramine HCL 2%

Zinc acetate 0.1%

Purpose

External analgesic

Skin protectant

Uses

- for the temporary relief of pain and itching associated with minor skin irritations
- dries the oozing and weeping of poison: ivy, oak, sumac

Warnings

For external use only

Flammable. Keep away from fire or flame.

Do not use

- on large areas of the body
- with any other product containing diphenhydramine, even one taken by mouth

Ask a doctor before use

on chicken pox or measles

When using this product

do not get in eyes

Stop use and ask a doctor if

condition worses or symptoms last more than 7 days or clear up and occur again within a few days.

Keep out of reach of children.

If swallowed, get medical help or contact a Poison Control Center right away.

Directions

- do not use more than directed
- adults and children 2 years of age and older: apply to affected area not more than 3 to 4 times daily
- children under 2 years of age: ask a doctor

Other information

store at 20⁰ to 25⁰ C (68⁰ to 77⁰ F)

Inactive ingredients

alcohol, glycerin, povidone, purified water, tris (hydroxymethyl) aminomethane

ADVERSE REACTIONS

*Not manufactured or distributed by Johnson & Johnson Consumer Products Company, distributor of Benadryl®Spray.

DISTRIBUTED BY OLD EAST MAIN CO.

100 MISSION RIDE

GOODLETTSVILLE, TN 37072

principal display panel

TEAR HERE

DG™ health

Compare to active ingredents in Benadryl®Spray*

Itch Relief Spray

External Analgesic

Skin Protectant

Relieves itching due to insect bites, poison oak or ivy, or other minor skin irritations

100% Satisfaction Guaranteed! (888)309-9030

2 FL OZ (59 mL)